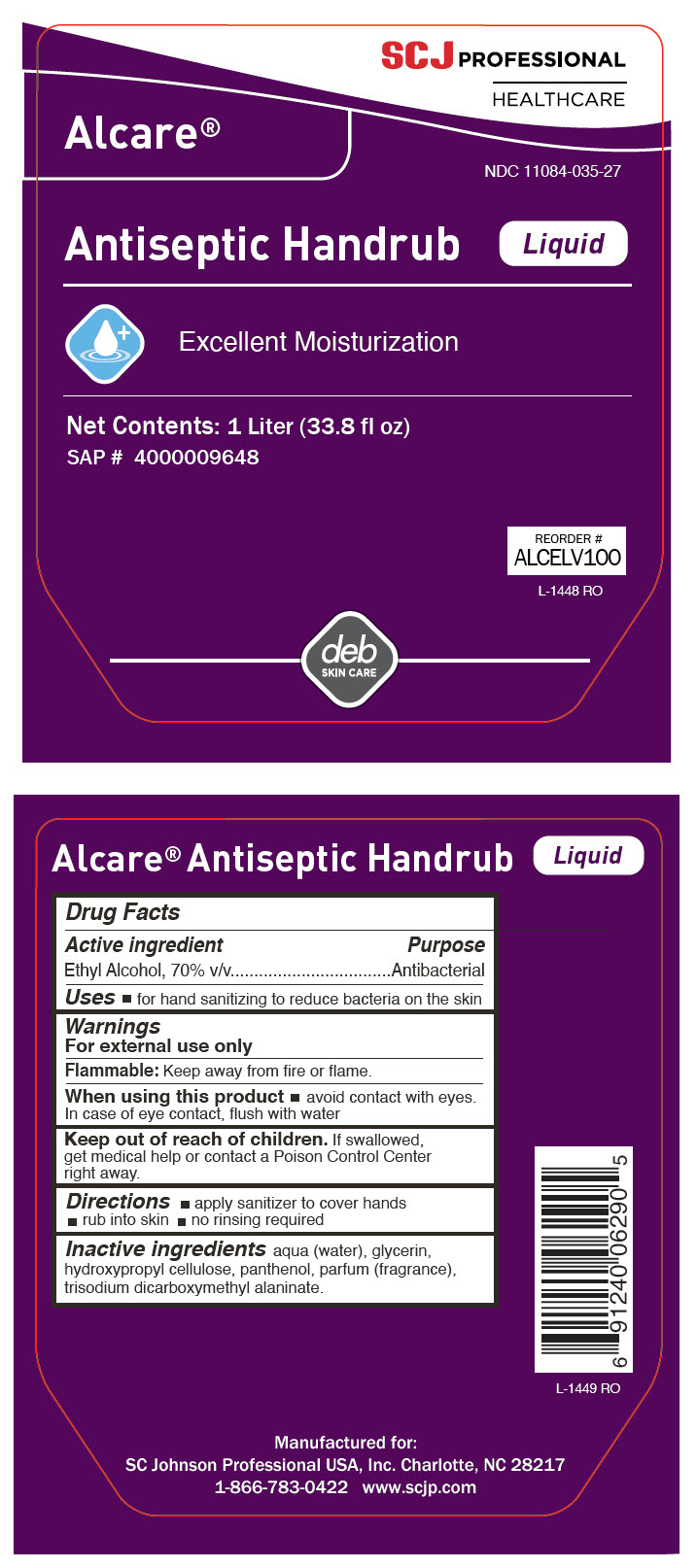 DRUG LABEL: Alcare Antiseptic Handrub
NDC: 11084-035 | Form: LIQUID
Manufacturer: SC Johnson Professional USA, Inc.
Category: otc | Type: HUMAN OTC DRUG LABEL
Date: 20251222

ACTIVE INGREDIENTS: ALCOHOL 70 mL/100 mL
INACTIVE INGREDIENTS: WATER; GLYCERIN; HYDROXYPROPYL CELLULOSE (1600000 WAMW); PANTHENOL; TRISODIUM DICARBOXYMETHYL ALANINATE

Alcare® Liquid Antiseptic Handrub

Drug Facts

Active ingredient

Ethyl Alcohol, 70% v/v

Purpose

Antibacterial

Uses

- for hand sanitizing to reduce bacteria on the skin

Warnings

For external use only

Flammable: Keep away from ﬁre or ﬂame.

When using this product

- avoid contact with eyes. In case of eye contact, ﬂush with water

Keep out of reach of children. If swallowed, get medical help or contact a Poison Control Center right away.

Directions

- apply sanitizer to cover hands
- rub into skin
- no rinsing required

Inactive ingredients

aqua (water), glycerin, hydroxypropyl cellulose, panthenol, parfum (fragrance), trisodium dicarboxymethyl alaninate.

PRINCIPAL DISPLAY PANEL - 1 Liter Bottle Label

SCJ PROFESSIONAL
HEALTHCARE

Alcare®

NDC 11084-035-27

Antiseptic Handrub Liquid

Excellent Moisturization

Net Contents: 1 Liter (33.8 fl oz)
SAP # 4000009648

REORDER #
ALCELV100
L-1448 RO

deb
SKIN CARE